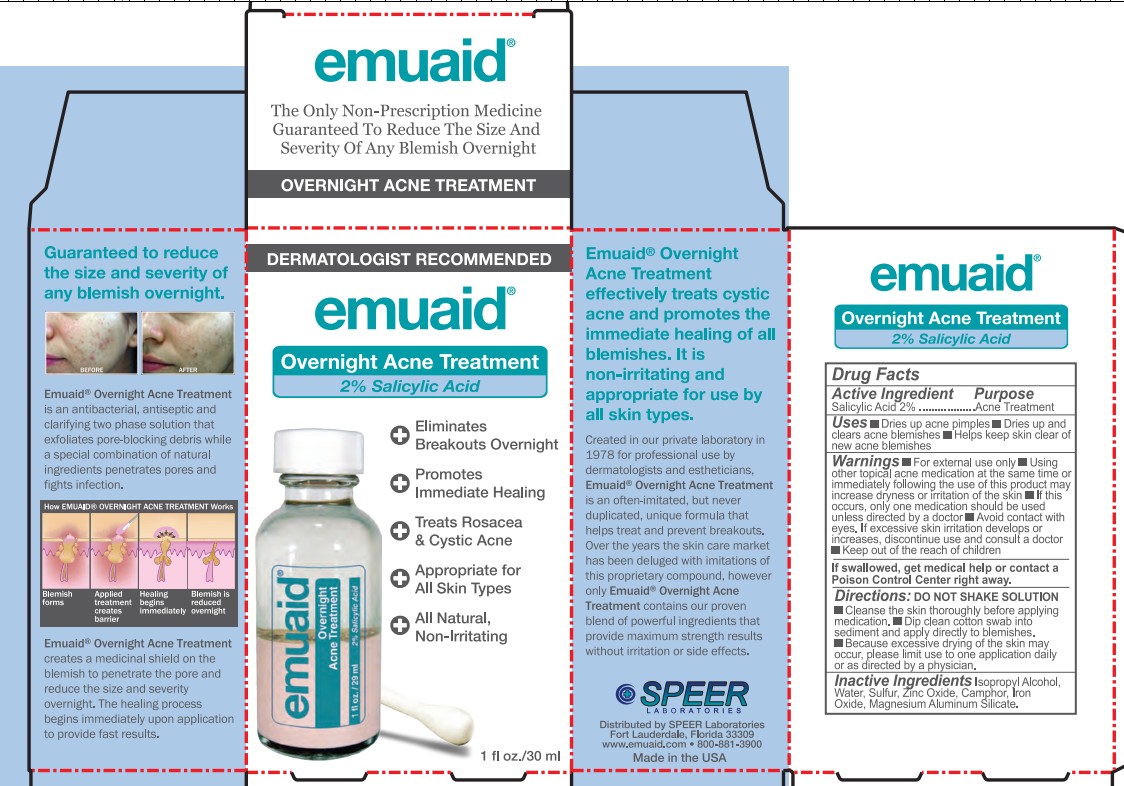 DRUG LABEL: Emuaid
NDC: 55926-0029 | Form: LIQUID
Manufacturer: Speer Laboratories, LLC
Category: otc | Type: HUMAN OTC DRUG LABEL
Date: 20260123

ACTIVE INGREDIENTS: Salicylic Acid 2 g/100 mL
INACTIVE INGREDIENTS: Isopropyl alcohol; Water; Sulfur; Zinc Oxide; CAMPHOR (NATURAL); FERRIC OXIDE RED; Magnesium Aluminum Silicate

Active Ingredient

Salicylic Acid 2%

Purpose

Acne Treatment

Uses

• Dries up acne pimples
• Dries up and clear acne blemishes
• Helps keep skin clear of new acne blemishes

Warnings

• For external use only

• Using other topical acne medication at the same time or immediately following the use of this product pay increase dryness or irritation of the skin
• If this occurs, only one medication should be used unless directed by a doctor
• Avoid contact with eyes.
• If excessive skin irritation develops or increases, discontinue use and consult a doctor.

Keep out of reach of children. If swallowed, get medical help or contact a Poison Control Center right away

Directions

DO NOT SHAKE SOLUTION
• Cleanse the skin thoroughly before applying medication.
• Dip clean cotton swab into sediment and apply directly to blemishes.
• Because excessive drying of the skin may occur, please limit use to one application daily or as directed by a physician.

Inactive Ingredients

Isopropyl alcohol, Water, Sulfur, Zinc Oxide, Camphor, Iron Oxide, Magnesium Aluminum Silicate

emuaid®

The Only Non-Prescription Medicine Guaranteed To Reduce The Size And Severity of Any Blemish Overnight

OVERNIGHT ACNE TREATMENT

Guaranteed to reduce the size and severity of any blemish overnight.

Emuaid® Overnight Acne Treatment is an antibacterial, antiseptic and clarifying two phase solution that exfoliates pore-blocking debris while a special combination of natural ingredients penetrates pores and fights infection.

Emuaid® Overnight Acne Treatment creates a medicinal shield on the blemish to penetrate the pore and reduce the size and severity overnight. The healing process begins immediately upon application to provide fast results.

Emuaid® Overnight Acne Treatment effectively treats cystic acne and promotes immediate healing of all blemishes. It is non-irritating and appropriate for use by all skin types.

Created in our private laboratory in 1978 for professional use by dermatologists and estheticians, Emuaid® Overnight Acne Treatment, is an often-imitated, but never duplicated, unique formula that helps treat and prevent breakouts. Over the years the skin care market has been deluged with imitations of this proprietary compound, however only Emuaid® Overnight Acne Treatment contains our proven blend of powerful ingredients that provide maximum strength results without irritation or side effects.

Speer Laboratories
Distributed by Speer Laboratories
Fort Lauderdale, Florida 33309
www.emuaid.com • 800-831-3900
Made in USA

PACKAGE LABEL

DETMATOLOGIST RECOMMENDED

Emuaid®

Overnight Acne Treatment
2% Salicylic Acid

Eliminates Breakouts Overnight

Promotes Immediate Healing

Treats Rosacea & Cystic Ance

Appropriate for All Skin Types

All Natural, Non-Irritating

1 fl. oz./30 mL